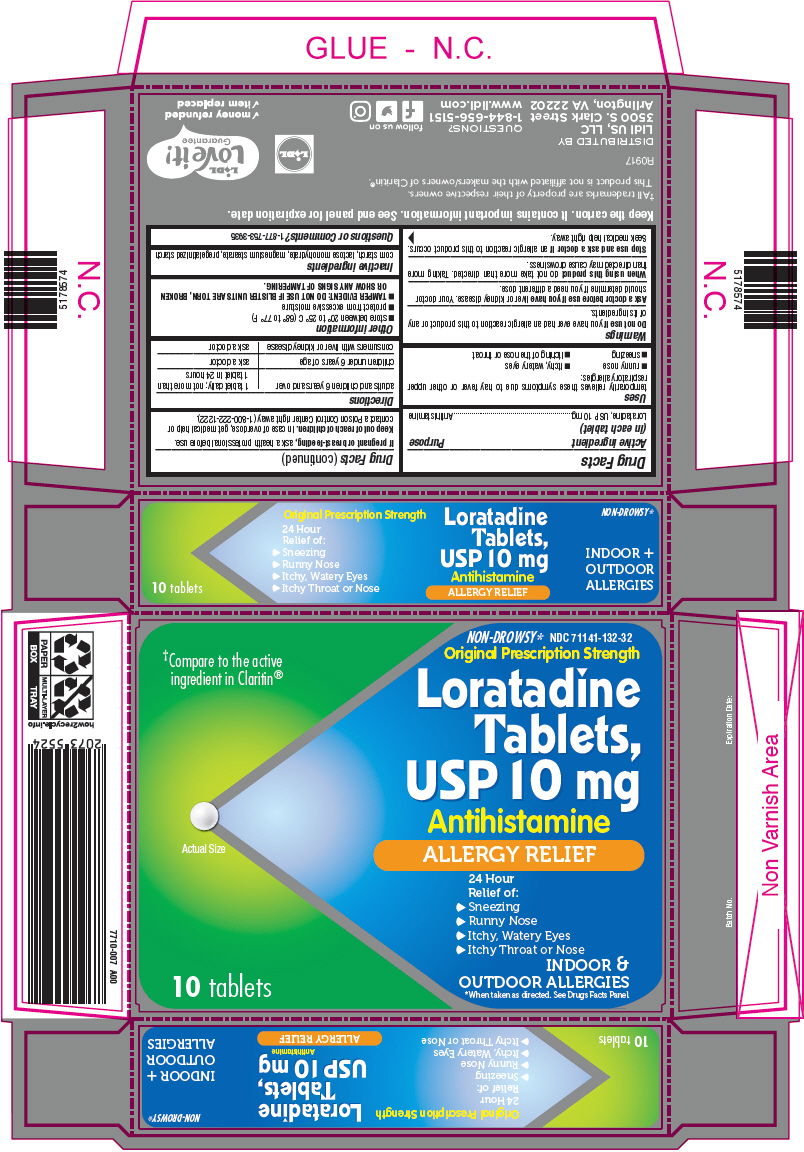 DRUG LABEL: Loratadine Allergy Relief
NDC: 71141-132 | Form: TABLET
Manufacturer: LIDL US, LLC
Category: otc | Type: HUMAN OTC DRUG LABEL
Date: 20180109

ACTIVE INGREDIENTS: LORATADINE 10 mg/1 1
INACTIVE INGREDIENTS: STARCH, CORN; LACTOSE MONOHYDRATE; MAGNESIUM STEARATE

Drug Facts

ACTIVE INGREDIENT(S)

Loratadine USP, 10 mg

PURPOSE

Antihistamine

USE(S)

Temporarily relieves these symptoms due to hay fever or other upper respiratory allergies:

- runny nose
- itchy, watery eyes
- sneezing
- itching of the nose or throat

WARNINGS

Do not use

If you have ever had an allergic reaction to this product or any of its ingredients.

Ask a doctor before use if you have

Liver or kidney disease. Your doctor should determine if you need a different dose.

When using this product

Do not take more than directed. Taking more than directed may cause drowsiness.

Stop use and ask a doctor if

An allergic reaction to this product occurs. Seek medical help right away.

If pregnant or breast-feeding,

Ask a health professional before use.

Keep out of reach of children.

In case of overdose, get medical help or contact a Poison Control Center right away.

DIRECTIONS

adults and children 6 years and over | 1 tablet daily; not more than 1 tablet in 24 hours
children under 6 years of age | ask a doctor
consumers with liver and kidney disease | ask a doctor

OTHER INFORMATION

- store between 20 and 25° C (68 and 77° F)
- protect from excessive moisture
- TAMPER EVIDENT: DO NOT USE IF IMPRINTED SEAL IS BROKEN OR MISSING FROM BOTTLE.

INACTIVE INGREDIENTS

Corn starch, lactose monohydrate, magnesium stearate, pregelatinized starch

Questions or Comments?

1-877-753-3935

DISTRIBUTED BY
Lidl US, LLC
3500 S. Clark Street
Arlington, VA 22202

PRINCIPAL DISPLAY PANEL - 10 mg Tablet Blister Pack Carton

NON-DROWSY* NDC 71141-132-32

Original Prescription Strength

†Compare to the active
ingredient in Claritin®

Actual Size

Loratadine
Tablets,
USP 10 mg

Antihistamine

ALLERGY RELIEF

24 Hour
Relief of:

▶ Sneezing
▶ Runny Nose
▶ Itchy, Watery Eyes
▶ Itchy Throat or Nose

10 tablets

INDOOR &
OUTDOOR ALLERGIES
*When taken as directed. See Drugs Facts Panel.